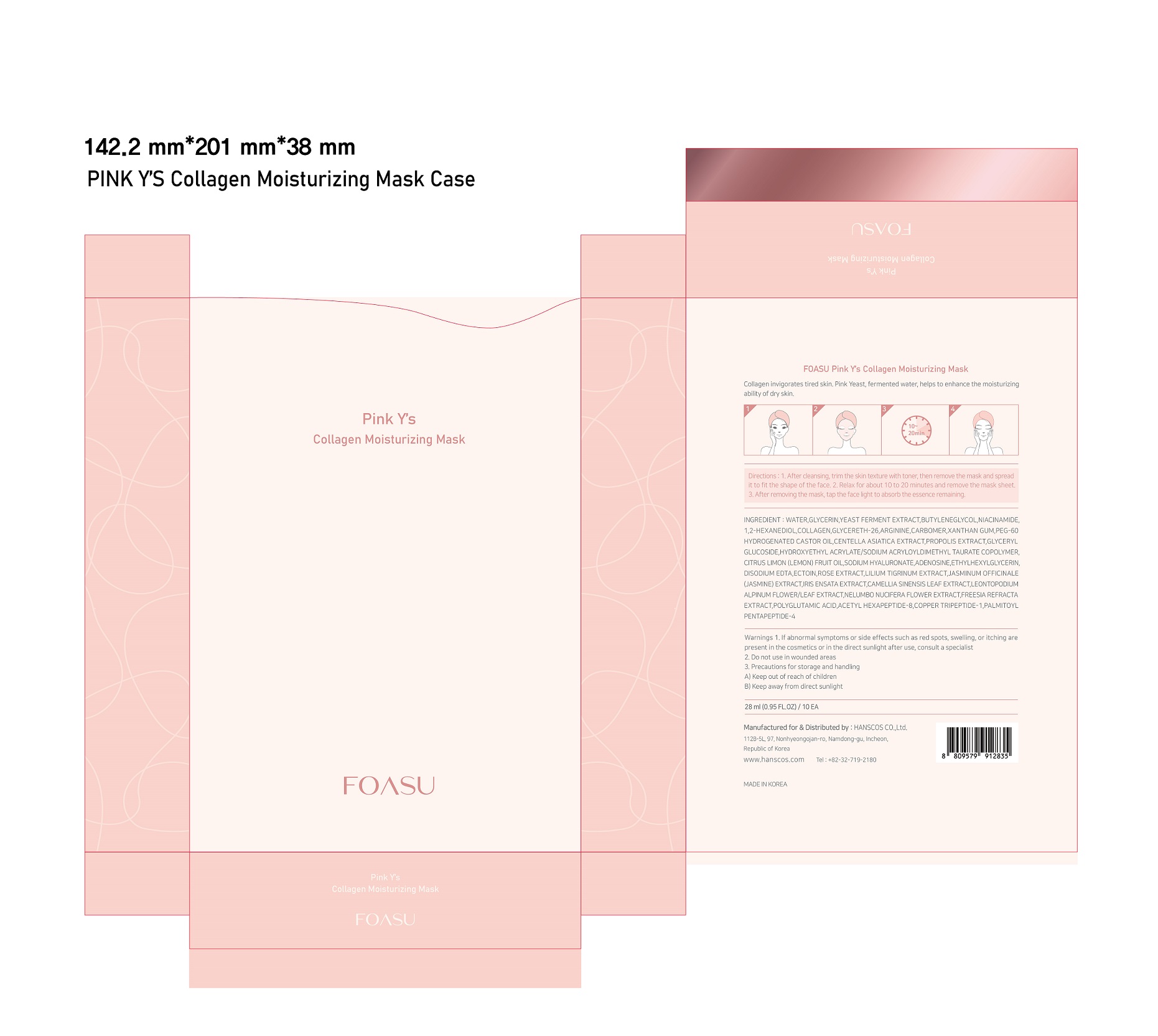 DRUG LABEL: FOASU Pink Y s Collagen Moisturizing Mask
NDC: 77964-006 | Form: LIQUID
Manufacturer: HANSCOS Co.,Ltd.
Category: otc | Type: HUMAN OTC DRUG LABEL
Date: 20220227

ACTIVE INGREDIENTS: ADENOSINE 0.04 g/100 mL; NIACINAMIDE 2 g/100 mL
INACTIVE INGREDIENTS: WATER; GLYCERIN

Active ingredient

niacinamide, adenosine

Purpose

skin protectant

Use

- after cleansing, trim the skin texture with toner, then remove the mask and spread it it fit the shape of the face

- relax for about 10 to 20 minutes and remove the mask sheet

- after removing the mask, tap the face light to absorb the essence remaining

Warnings

For external use only

1) Please consult your doctor if you experience side effects such as swelling, itching, or reddening on the area where you applied this product

2) Do not apply on wounds or cuts. 3) Do not store where children may reach, and avoid keeping it exposed to direct sunlight.

Directions

for external use only

Inactive ingredients

WATER
GLYCERIN
YEAST FERMENT EXTRACT
BUTYLENEGLYCOL
1,2-HEXANEDIOL
COLLAGEN
GLYCERETH-26
ARGININE
CARBOMER
XANTHAN GUM
PEG-60 HYDROGENATED CASTOR OIL
CENTELLA ASIATICA EXTRACT
PROPOLIS EXTRACT
GLYCERYL GLUCOSIDE
HYDROXYETHYL ACRYLATE/SODIUM ACRYLOYLDIMETHYL TAURATE COPOLYMER
CITRUS LIMON (LEMON) FRUIT OIL
SODIUM HYALURONATE
ETHYLHEXYLGLYCERIN
DISODIUM EDTA
ECTOIN
ROSE EXTRACT
LILIUM TIGRINUM EXTRACT
JASMINUM OFFICINALE (JASMINE) EXTRACT
IRIS ENSATA EXTRACT
CAMELLIA SINENSIS LEAF EXTRACT
LEONTOPODIUM ALPINUM FLOWER/LEAF EXTRACT
NELUMBO NUCIFERA FLOWER EXTRACT
FREESIA REFRACTA EXTRACT
POLYGLUTAMIC ACID
ACETYL HEXAPEPTIDE-8
COPPER TRIPEPTIDE-1
PALMITOYL PENTAPEPTIDE-4

Keep out of reach of children. If swallowed, get medical help or contact a Poison Control Center right away.